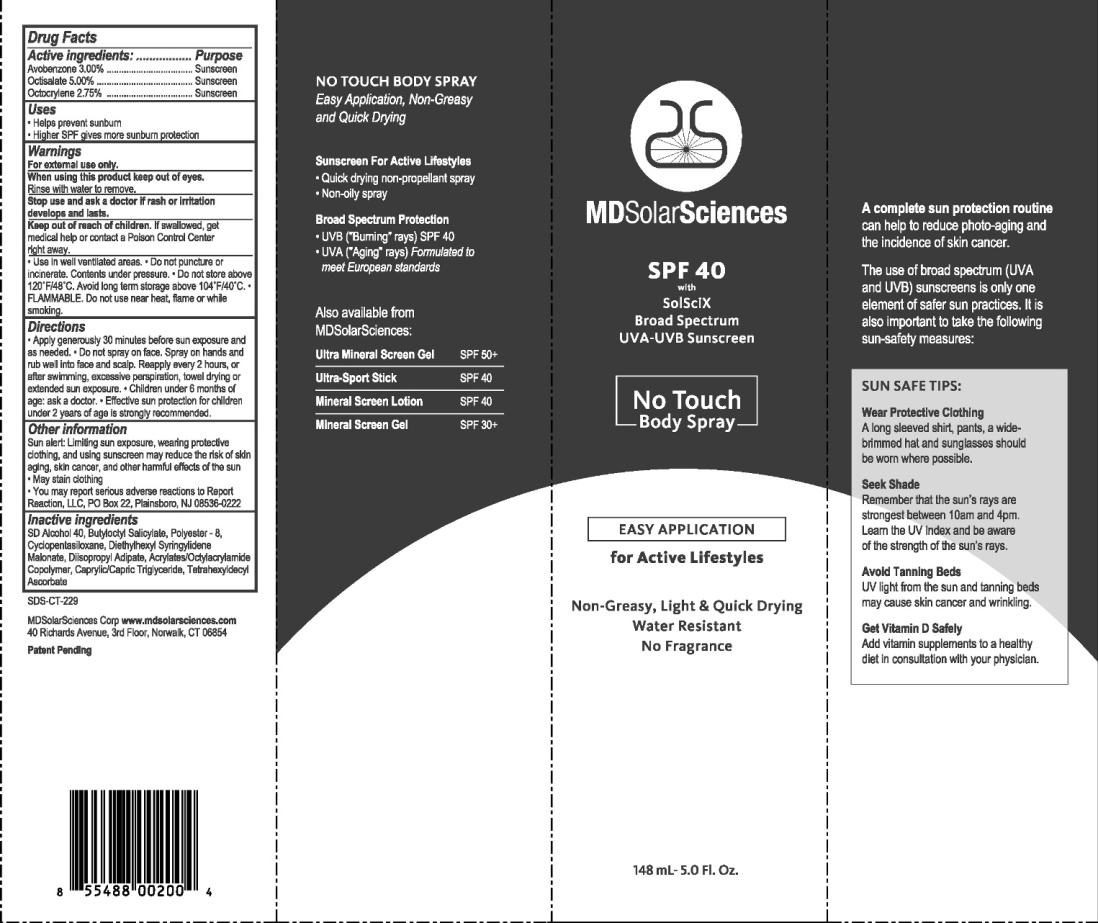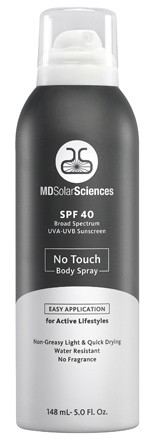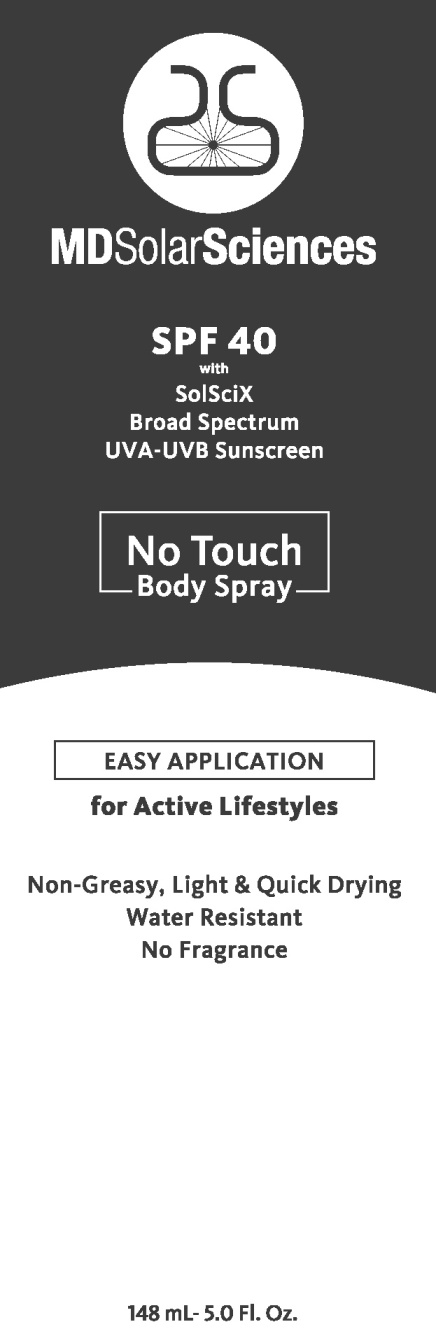 DRUG LABEL: MDSolarSciences SPF40 No Touch Body
NDC: 17452-370 | Form: SPRAY
Manufacturer: Ecometics, Inc
Category: otc | Type: HUMAN OTC DRUG LABEL
Date: 20101015

ACTIVE INGREDIENTS: Avobenzone 3 g/100 mL; Octisalate 5 g/100 mL; Octocrylene 2.75 g/100 mL
INACTIVE INGREDIENTS: Alcohol; Butyloctyl salicylate; POLYESTER-8 (1400 MW, CYANODIPHENYLPROPENOYL CAPPED); Diisopropyl Adipate; Tetrahexyldecyl Ascorbate; CYCLOMETHICONE 5

Drug Facts

Active Igredients

Avobenzone 3.00% .............Sunscreen

Octisalate 5.00% ...................Sunscreen

Octocrylene 2.75% ............... Sunscreen

Uses

Helps prevent sunburn
Higher SPF gives more sunburn protection

Warnings

For external uses only.
When using this product keep out of eyes.
Rinse with water to remove.
Stop use and ask a doctor if rash or irritation develops and lasts.
use in well ventilated areas.
Do not puncture or incinerate.
Contents under pressure.
Do not store above 1200F/480C.
Avoid long term storage above 1040F/400C.
FLAMMABLE.
Do not use near heat, flame or while smoking.

Directions

Apply generously 30 minutes before sun exposure and as needed.
Do not spray on face.
Spray on hands and rub well into face and scalp.
Reapply every 2 hours, or after swimming, excessive perspiration, towel drying or extended sun exposure.
Children under 6 months of age: ask a doctor.
Effective sun protection for children under 2 years of age is strongly recommended.

Other Information

Sun alert: Limiting sun exposure, wearing protective clothing, and using sunscreen may reduce the risk of skin aging, skin cancer, and other harmful effects of the sun.
May stain clothing.
You may report serious adverse reactions to Report Reactions, LLC, PO Box 22, Plainsboro, NJ 08536-0222

Inactive Ingredients

SD Alcohol 40, Butyloctyl Salicylate, Polyester-8, Cyclopentasiloxane, Diethylhexyl Syringylidene Malonate, Diisopropyl Adipate, Acrylates/Octylacrylamides Copolymer, Caprylic/Capric Triglyceride, Tetrahexyldecyl Ascorbate

Principle Display Panel

MDSolarSciences
SPF 40
with
SolSciX
Broad Spectrum
UVA-UVB Sunscreen
No Touch
Body Spray
EASY APPLICATION
for Active Lifestyles
Non-Greasy, Light and Quick Drying
148 mL-5.0 Fl.Oz.

Additional Carton Labeling

NO TOUCH BODY SPRAY
Easy Application, Non-Greasy and Quick Drying
Sunscreen For Active Lifestyles
Quick drying non-propellant spray
Non-oily spray
Broad Spectrum Protection
UVB ("Buring" rays" SPF 40
UVA ("Aging" rays) Formulated to meet European standards
Also available from MDSolarSciences:
Ultra Mineral Screeen Gel SPF 50+
Ultra-Sport Stick SPF 40
Mineral Screen Lotion SPF 40
Mineral Screen Gel SPF 30+
SDS-CT-229
MDSolarSciences Corp www.mdsolarsciences.com
40 Richards Avenue, 3rd Floor, Norwalk, CT 06854
Patent Pending
UPC 8 55488 00200 4
A complete sun protection routine
can help to reduce photo-aging and
the incidence of skin cancer.
The use of broad spectrum (UVA
and UVB) sunscreens is only one
element of safer sun practices. It is
also important to take the following
sun-safety measures:
SUN SAFE TIPS:
Wear Protective Clothing
A long sleeved shirt, pants, a wide-
brimmed har and sunglasses should
be worn where possible
Seek Shade
Remember that the sun's rays are
strongest between 10am and 4pm.
Learn the UV Index and be aware
of the strength of the sun's rays.
Avoid Tanning Beds
UV light from the sun and tanning beds
may cause skin cancer and wrinkling
Get Vitamin D Safely
Add vitamin supplements to a healthy
dient in consultation with your physician.